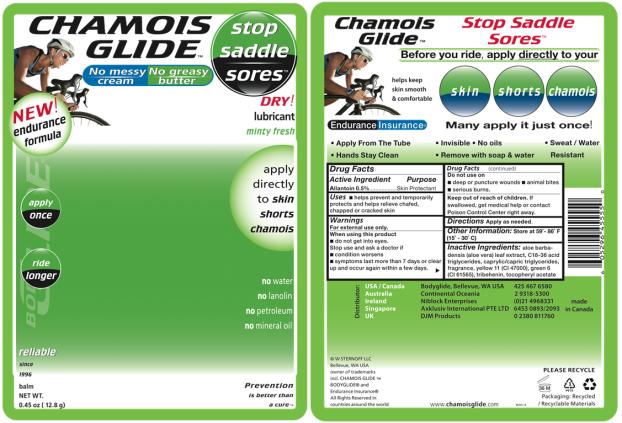 DRUG LABEL: Chamois Glide
NDC: 15197-008 | Form: STICK
Manufacturer: W STERNOFF LLC
Category: otc | Type: HUMAN OTC DRUG LABEL
Date: 20091206

ACTIVE INGREDIENTS: ALLANTOIN 5 mg/1 g
INACTIVE INGREDIENTS: ALOE VERA LEAF; D&C YELLOW NO. 11; D&C GREEN NO. 6; .ALPHA.-TOCOPHEROL ACETATE, D-; TRIBEHENIN; MEDIUM-CHAIN TRIGLYCERIDES

Chamois Glide

Active Ingredient:

Allantoin 0.5%

Purpose

Skin Protectant

Uses

- helps prevent and helps relieve chafed, chapped or cracked skin
- helps protect from the drying effects of wind and cold weather
- temporarily protects minor cuts, scrapes, burns

Warnings

For external use only.

When using this product

- do not get into eyes

Stop use and ask a doctor if

- condition worsens
- symptoms last more than 7 days or clear up and occur again within a few days

Do not use on

- deep or puncture wounds
- animal bites
- serious burns

Keep out of reach of children. If swallowed, get medical help or contact Poison Control Center right away.

Directions

Apply as needed.

Inactive Ingredients

aloe barbadensis leaf juice, C18-36 acid triglyceride, capric/caprylic triglycerides, fragrance, yellow 11 (CI 47000), green 6 (CI 61565), tocopheryl acetate, tribehenin

Questions +1 425.467.6580

Distributor: Bodyglide, Bellevue, WA USA

© 2009 W Sternoff LLC Made in Canada

Principal Display Panel

minty fresh

new endurance formula

apply directly to skin, shorts, chamois
stop saddle sores™

No messy cream

No greasy butter

invisible

no water

no lanolin

no petroleum

no mineral oil

reliable since 1996

apply once

ride longer

NET WT. 0.45 oz (12.8 g)